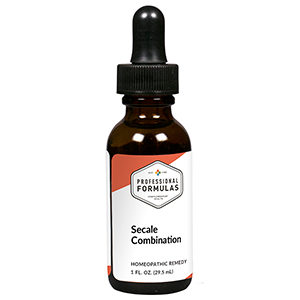 DRUG LABEL: Secale Combination
NDC: 63083-9244 | Form: LIQUID
Manufacturer: Professional Complementary Health Formulas
Category: homeopathic | Type: HUMAN OTC DRUG LABEL
Date: 20190815

ACTIVE INGREDIENTS: OYSTER SHELL CALCIUM CARBONATE, CRUDE 4 [hp_X]/29.5 mL; CLAVICEPS PURPUREA SCLEROTIUM 4 [hp_X]/29.5 mL; SOLANUM NIGRUM TOP 4 [hp_X]/29.5 mL; AVISCUMINE 4 [hp_X]/29.5 mL; SILVER NITRATE 6 [hp_X]/29.5 mL; BARIUM IODIDE 6 [hp_X]/29.5 mL; PHOSPHORUS 8 [hp_X]/29.5 mL; TOBACCO LEAF 8 [hp_X]/29.5 mL; ARNICA MONTANA WHOLE 12 [hp_X]/29.5 mL; ARSENIC TRIOXIDE 12 [hp_X]/29.5 mL
INACTIVE INGREDIENTS: ALCOHOL; WATER

R244

ACTIVE INGREDIENTS

Calcarea carbonica 4X
Secale cornutum 4X
Solanum nigrum 4X
Viscum album 4X
Argentum nitricum 6X
Baryta iodata 6X
Phosphorus 8X
Tabacum 8X
Arnica montana 12X
Arsenicum album 12X

QUESTIONS

Professional Formulas

PO Box 2034 Lake Oswego, OR 97035

INDICATIONS

For the temporary relief of exhaustion, generalized weakness, or coldness of extremities.*

PURPOSE

*Claims based on traditional homeopathic practice, not accepted medical evidence. Not FDA evaluated.

WARNINGS

Consult a doctor if condition worsens or if symptoms persist. Keep out of the reach of children. In case of overdose, get medical help or contact a poison control center right away. If pregnant or breastfeeding, ask a healthcare professional before use.

Keep out of the reach of children.

PREGNANCY OR BREAST FEEDING

If pregnant or breastfeeding, ask a healthcare professional before use.

DIRECTIONS

Place drops under tongue 30 minutes before/after meals. Adults and children 12 years and over: Take 10 drops up to 3 times per day. Consult a physician for use in children under 12 years of age.

OTHER INFORMATION

Tamper resistant. If seal is broken, do not use. After opening, close container tightly and store at room temperature away from heat.

INACTIVE INGREDIENTS

40% ethanol, purified water.

LABEL

Est 1985

Professional Formulas

Complementary Health

Secale Combination

Homeopathic Remedy

1 FL. OZ. (29.5 mL)